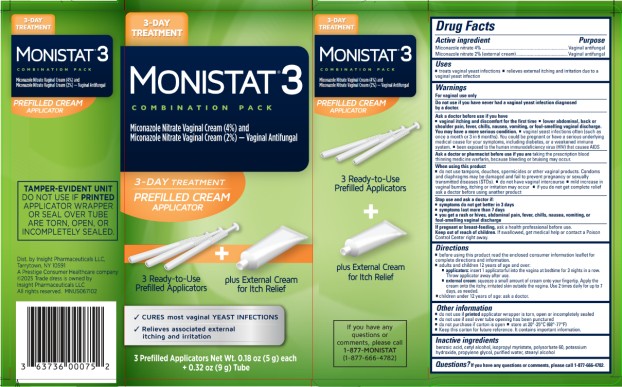 DRUG LABEL: Monistat 3 Combination Pack
NDC: 63736-010 | Form: KIT | Route: VAGINAL
Manufacturer: Insight Pharmaceuticals LLC
Category: otc | Type: HUMAN OTC DRUG LABEL
Date: 20251027

ACTIVE INGREDIENTS: MICONAZOLE NITRATE 40 mg/1 g; Miconazole Nitrate 10 mg/0.5 g
INACTIVE INGREDIENTS: BENZOIC ACID; CETYL ALCOHOL; ISOPROPYL MYRISTATE; POLYSORBATE 60; POTASSIUM HYDROXIDE; PROPYLENE GLYCOL; WATER; STEARYL ALCOHOL; Benzoic Acid; Cetyl Alcohol; Isopropyl Myristate; Polysorbate 60; Potassium Hydroxide; Propylene glycol; Water; Stearyl Alcohol

MONISTAT 3 Combination Pack - 63736-010

DRUG FACTS

Active ingredients

Miconazole nitrate 4%
Miconazole nitrate 2% (external cream)

Purpose

Vaginal antifungal
Vaginal antifungal

Uses

- treats vaginal yeast infections
- relieves external itching and irritation due to a vaginal yeast infection

Warnings

For vaginal use only

Do not use

if you have never had a vaginal yeast infection diagnosed by a doctor.

Ask a doctor before use if you have

- vaginal itching and discomfort for the first time
- lower abdominal, back or shoulder pain, fever, chills, nausea, vomiting, or foul-smelling vaginal discharge. You may have a more serious condition.
- vaginal yeast infections often (such as once a month or 3 in 6 months). You could be pregnant or have a serious underlying medical cause for your symptoms, including diabetes or a weakened immune system.
- been exposed to the human immunodeficiency virus (HIV) that causes AIDS

Ask a doctor or pharmacist before use if you are

taking the prescription blood thinning medicine warfarin, because bleeding or bruising may occur

When using this product

- do not use tampons, douches, spermicides or other vaginal products. Condoms and diaphragms may be damaged and fail to prevent pregnancy or sexually transmitted diseases (STDs).
- do not have vaginal intercourse
- mild increase in vaginal burning, itching or irritation may occur
- if you do not get complete relief ask a doctor before using another product

Stop use and ask a doctor if

- symptoms do not get better in 3 days
- symptoms last more than 7 days
- you get a rash or hives, abdominal pain, fever, chills, nausea, vomiting, or foul-smelling vaginal discharge

If pregnant or breast-feeding,

ask a health professional before use.

Keep out of reach of children.

If swallowed, get medical help or contact a Poison Control Center right away.

Directions

- before using this product read the enclosed consumer information leaflet for complete directions and information
- adults and children 12 years of age and over:
- applicators: insert 1 applicatorful into the vagina at bedtime for 3 nights in a row. Throw away applicator after use.
- external cream: squeeze a small amount of cream onto your fingertip. Apply the cream onto the itchy, irritated skin outside the vagina. Use 2 times daily for up to 7 days, as needed.
- children under 12 years of age: ask a doctor

Other information

- do not use if printed applicator wrapper is torn, open or incompletely sealed
- do not use if seal over tube opening has been punctured
- do not purchase if carton is open
- store at 20°-25°C (68°-77°F)
- Keep this carton for future reference. It contains important information.

Inactive ingredients

benzoic acid, cetyl alcohol, isopropyl myristate, polysorbate 60, potassium hydroxide, propylene glycol, purified water, stearyl alcohol

Questions?

If you have any questions or comments, please call 1-877-666-4782

PRINCIPAL DISPLAY PANEL

- Kit Carton

MONISTAT® 3

COMBINATION PACK

Miconazole Nitrate Vaginal Cream (4%) and Miconazole Nitrate Cream (2%) - Vaginal Antifungal

3 PREFILLED APPLICATORS Net Wt. 0.18 oz. (5g) +0.32 oz. (9g) tube